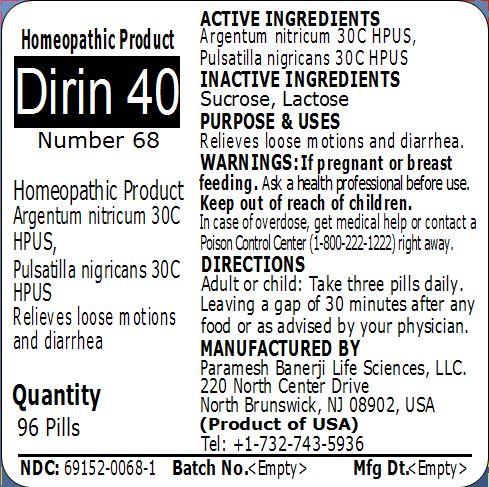 DRUG LABEL: Dirin 40 (Number 68)
NDC: 69152-0068 | Form: PELLET
Manufacturer: Paramesh Banerji Life Sciences LLC
Category: homeopathic | Type: HUMAN OTC DRUG LABEL
Date: 20150307

ACTIVE INGREDIENTS: PULSATILLA PRATENSIS 30 [hp_C]/1 1; SILVER NITRATE 30 [hp_C]/1 1
INACTIVE INGREDIENTS: SUCROSE; LACTOSE

Active Ingredients

Argentum nitricum 30C HPUS, Pulsatilla nigricans 30C HPUS

Inactive Ingredients

Sucrose, Lactose

Purpose

Relieves loose motions and diarrhea

Uses

Relieves loose motions and diarrhea

Warnings

If pregnant or breast feeding ask a health professional before use.

Keep out of reach of children. In case of overdose, get medical help or contact a Poison Control Center (1-800-222-1222) right away.

Direction

Adult or child: Take three pills daily. Leaving a gap of 30 minutes after any food or as advised by your physician.

Manufactured by

Paramesh Banerji Life Sciences, LLC

220 North Center Drive

North Brunswick, NJ 08902, USA

Product of USA

Tel: +1-732-743-5936

Principal Display Panel

Homeopathic Product

Dirin 40

Number 68

Homeopathic Product

Argentum nitricum 30C HPUS, Pulsatilla nigricans 30C HPUS

Relieves loose motions and diarrhea

Quantity

96 Pills